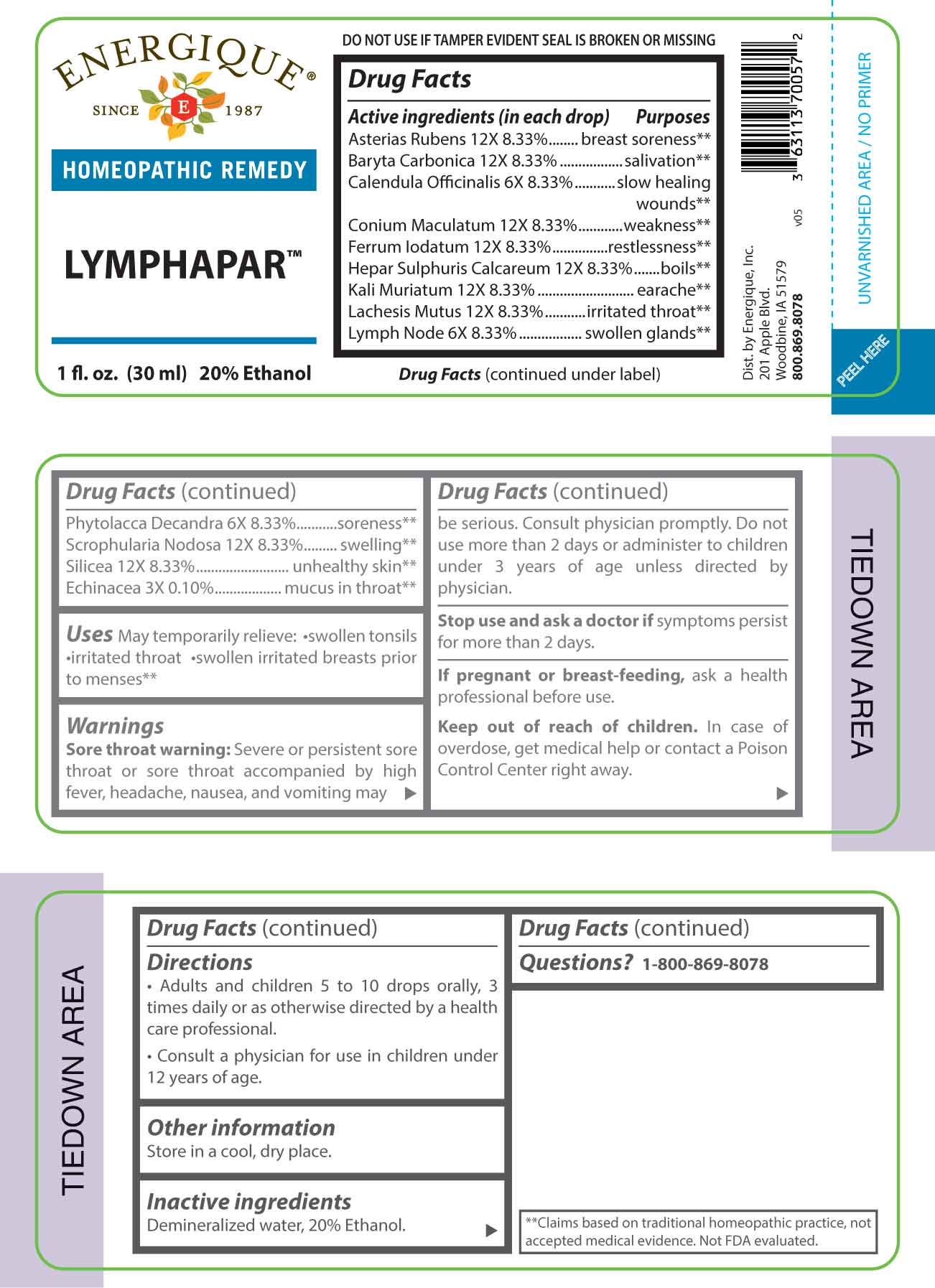 DRUG LABEL: Lymphapar
NDC: 44911-0707 | Form: LIQUID
Manufacturer: Energique, Inc.
Category: homeopathic | Type: HUMAN OTC DRUG LABEL
Date: 20240920

ACTIVE INGREDIENTS: ECHINACEA ANGUSTIFOLIA WHOLE 3 [hp_X]/1 mL; CALENDULA OFFICINALIS FLOWERING TOP 6 [hp_X]/1 mL; SUS SCROFA LYMPH 6 [hp_X]/1 mL; PHYTOLACCA AMERICANA ROOT 6 [hp_X]/1 mL; ASTERIAS RUBENS 12 [hp_X]/1 mL; BARIUM CARBONATE 12 [hp_X]/1 mL; CONIUM MACULATUM FLOWERING TOP 12 [hp_X]/1 mL; FERROUS IODIDE 12 [hp_X]/1 mL; CALCIUM SULFIDE 12 [hp_X]/1 mL; POTASSIUM CHLORIDE 12 [hp_X]/1 mL; LACHESIS MUTA VENOM 12 [hp_X]/1 mL; SCROPHULARIA NODOSA WHOLE 12 [hp_X]/1 mL; SILICON DIOXIDE 12 [hp_X]/1 mL
INACTIVE INGREDIENTS: WATER; ALCOHOL

DRUG FACTS:

ACTIVE INGREDIENTS:

Asterias Rubens 12X 8.33%, Baryta Carbonica 12X 8.33%, Calendula Officinalis 6X 8.33%, Conium Maculatum 12X 8.33%, Ferrum Iodatum 12X 8.33%, Hepar Sulphuris Calcareum 12X 8.33%, Kali Muriaticum 12X 8.33%, Lachesis Mutus 12X 8.33%, Lymph Node 6X 8.33%, Phytolacca Decandra 6X 8.33%, Scrophularia Nodosa 12X 8.33%, Silicea 12X 8.33%, Echinacea 3X 0.10%.

PURPOSE:

Asterias Rubens – breast soreness,** Baryta Carbonica - salivation,** Calendula Officinalis – slow healing wounds,** Conium Maculatum - weakness,** Ferrum Iodatum - restlessness,** Hepar Sulphuris Calcareum - boils,** Kali Muriaticum - earache,** Lachesis Mutus – irritated throat,** Lymph Node – swollen glands,** Phytolacca Decandra – soreness,** Scrophularia Nodosa - swelling,** Silicea – unhealthy skin,** Echinacea – mucus in throat**

**Claims based on traditional homeopathic practice, not accepted medical evidence. Not FDA evaluated.

USES:

May temporarily relieve: •swollen tonsils •irritated throat swollen irritated breasts prior to menses.**

**Claims based on traditional homeopathic practice, not accepted medical evidence. Not FDA evaluated.

WARNINGS:

Sore throat warning: Severe or persistent sore throat or sore throat accompanied by high fever, headache, nausea, and vomiting may be serious. Consult physician promptly. Do not use more than 2 days or administer to children under 3 years of age unless directed by physician.

Stop use and ask a doctor if symptoms persist for more than 2 days.

If pregnant or breast-feeding, ask a health professional before use.

Keep out of reach of children. In case of overdose, get medical help or contact a Poison Control Center right away.

DO NOT USE IF TAMPER EVIDENT SEAL IS BROKEN OR MISSING

KEEP OUT OF REACH OF CHILDREN:

In case of overdose, get medical help or contact a Poison Control Center right away.

DIRECTIONS:

• Adults and children 5 to 10 drops orally, 3 times daily or as otherwise directed by a health care professional.

• Consult a physician for use in children under 12 years of age.

INACTIVE INGREDIENTS:

Demineralized water, 20% Ethanol.

QUESTIONS:

Dist. by Energique, Inc.

201 Apple Blvd

Woodbine, IA 51579

800.869.8078

PACKAGE LABEL DISPLAY:

ENERGIQUE

SINCE 1987

HOMEOPATHIC REMEDY

LYMPHAPAR

1 fl. oz. (30 ml)